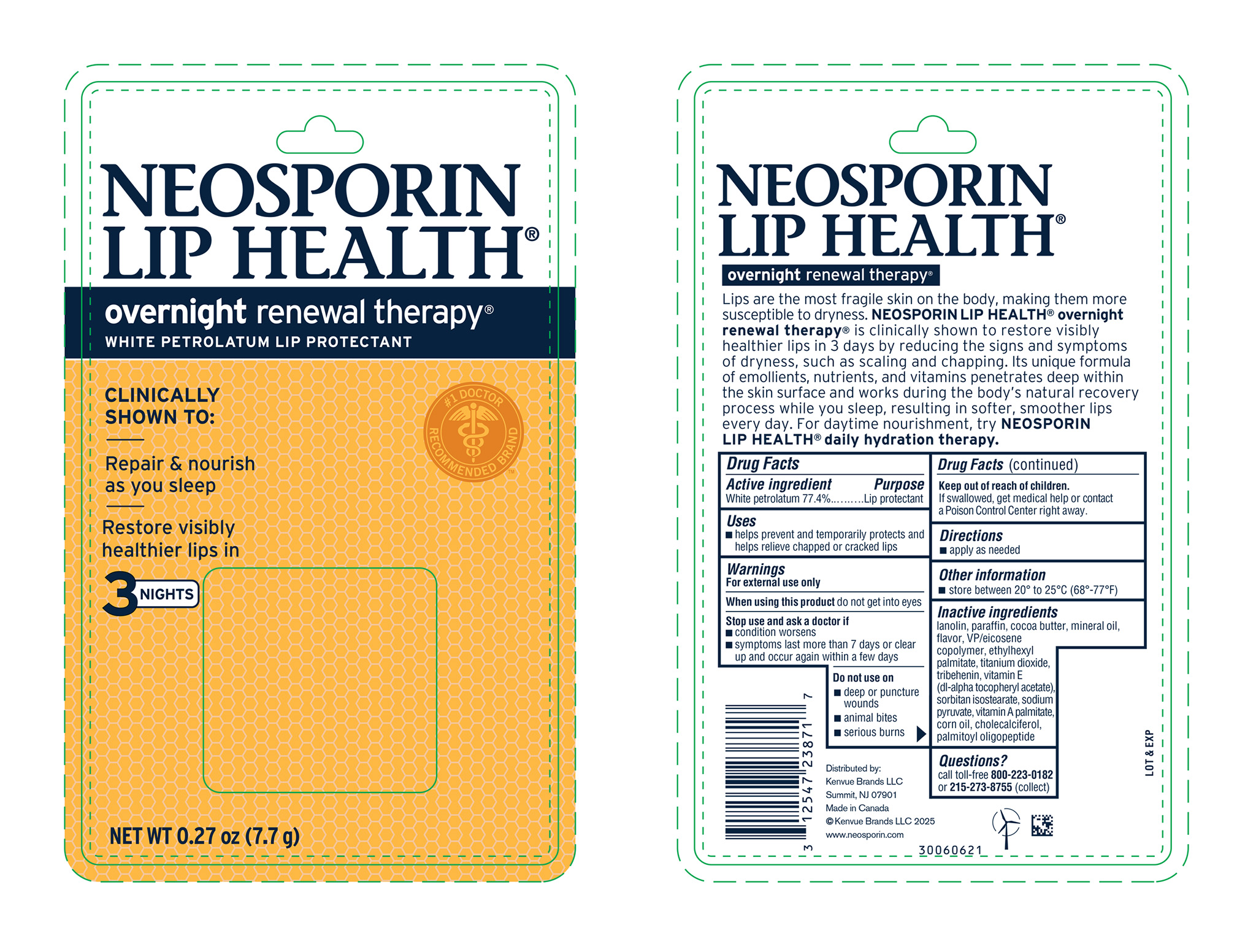 DRUG LABEL: Neosporin Lip Health
NDC: 69968-0208 | Form: OINTMENT
Manufacturer: Kenvue Brands LLC
Category: otc | Type: HUMAN OTC DRUG LABEL
Date: 20250710

ACTIVE INGREDIENTS: PETROLATUM 774 mg/1 g
INACTIVE INGREDIENTS: LANOLIN; PARAFFIN; COCOA BUTTER; MINERAL OIL; VINYLPYRROLIDONE/EICOSENE COPOLYMER; ETHYLHEXYL PALMITATE; TITANIUM DIOXIDE; TRIBEHENIN; .ALPHA.-TOCOPHEROL ACETATE; SORBITAN ISOSTEARATE; SODIUM PYRUVATE; VITAMIN A PALMITATE; CORN OIL; CHOLECALCIFEROL; PALMITOYL TRIPEPTIDE-1

NEOSPORIN LIP HEALTH® overnight renewal therapy®

Drug Facts

Active ingredient

White petrolatum 77.4%

Purpose

Lip protectant

Uses

- helps prevent and temporarily protects and helps relieve chapped or cracked lips

Warnings

For external use only

When using this product do not get into eyes

Stop use and ask a doctor if

- condition worsens
- symptoms last more than 7 days or clear up and occur again within a few days

Do not use on

- deep or puncture wounds
- animal bites
- serious burns

Keep out of reach of children.

If swallowed, get medical help or contact a Poison Control Center right away.

Directions

- apply as needed

Other information

- store between 20° to 25° C (68° - 77° F)

Inactive ingredients

lanolin, paraffin, cocoa butter, mineral oil, flavor, VP/eicosene copolymer, ethylhexyl palmitate, titanium dioxide, tribehenin , vitamin E (dl-alpha tocopheryl acetate), sorbitan isostearate, sodium pyruvate, vitamin A palmitate, corn oil, cholecalciferol, palmitoyl oligopeptide

Questions?

call toll-free 800-223-0182 or 215-273-8755 (collect)

Distributed by:

Kenvue Brands LLC
Summit, NJ 07901

PRINCIPAL DISPLAY PANEL - 7.7 g Jar Blister Pack

NEOSPORIN
LIP HEALTH ®

overnight renewal therapy®
WHITE PETROLATUM LIP PROTECTANT
#1 DOCTOR RECOMMENDED BRAND™
CLINICALLY
SHOWN TO:

Repair & nourish
as you sleep
Restore visibly
healthier lips in
3 NIGHTS

NET WT 0.27 oz (7.7g)